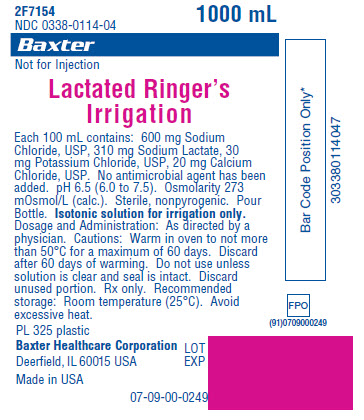 DRUG LABEL: Lactated Ringers
NDC: 0338-0114 | Form: IRRIGANT
Manufacturer: Baxter Healthcare Corporation
Category: prescription | Type: HUMAN PRESCRIPTION DRUG LABEL
Date: 20120612

ACTIVE INGREDIENTS: SODIUM CHLORIDE 600 mg/100 mL; SODIUM LACTATE 310 mg/100 mL; POTASSIUM CHLORIDE 30 mg/100 mL; CALCIUM CHLORIDE 20 mg/100 mL
INACTIVE INGREDIENTS: WATER

DESCRIPTION

Lactated Ringer’s Irrigation

Each 100 mL contains: 600 mg Sodium Chloride, USP, 310 mg Sodium Lactate, 30 mg Potassium Chloride, USP, 20 mg Calcium Chloride, USP. No antimicrobial agent has been added. pH 6.5 (6.0 to 7.5). Osmolarity 273 mOsmol/L (calc.). Sterile, nonpyrogenic. Pour Bottle.

INDICATIONS AND USAGE

Isotonic solution for irrigation only. Not for injection.

DOSAGE AND ADMINISTRATION

As directed by a physician.

Cautions: Warm in oven to not more than 50°C for a maximum of 60 days. Discard after 60 days of warming. Do not use unless solution is clear and seal is intact. Discard unused portion. Rx only.

HOW SUPPLIED

Recommended storage: Room temperature (25°C). Avoid excessive heat.

PRINCIPAL DISPLAY PANEL - PACKAGING LABELING

Container Label

Container Label

2F7154
NDC 0338-0114-04

1000 mL

Baxter Logo

Not for Injection

Lactated Ringer's
Irrigation

Each 100 mL contains: 600 mg Sodium
Chloride, USP, 310 mg Sodium Lactate, 30
mg Potassium Chloride, USP, 20 mg Calcium
Chloride, USP. No antimicrobial agent has been
added. pH 6.5 (6.0 to 7.5). Osmolarity 273
mOsmol/L (calc.). Sterile, nonpyrogenic. Pour
Bottle. Isotonic solution for irrigation only.
Dosage and Administration: As directed by a
physician. Cautions: Warm in oven to not more
than 50°C for a maximum of 60 days. Discard
after 60 days of warming. Do not use unless
solution is clear and seal is intact. Discard
unused portion. Rx only. Recommended
storage: Room temperature (25°C). Avoid
excessive heat.

PL 325 plastic

Baxter Healthcare Corporation
Deerfield, IL 60015 USA

Made in USA

LOT
EXP
FPO
(91)0709000249
Bar Code

07-09-00-0249

Bar Code Position Only*
303380114047